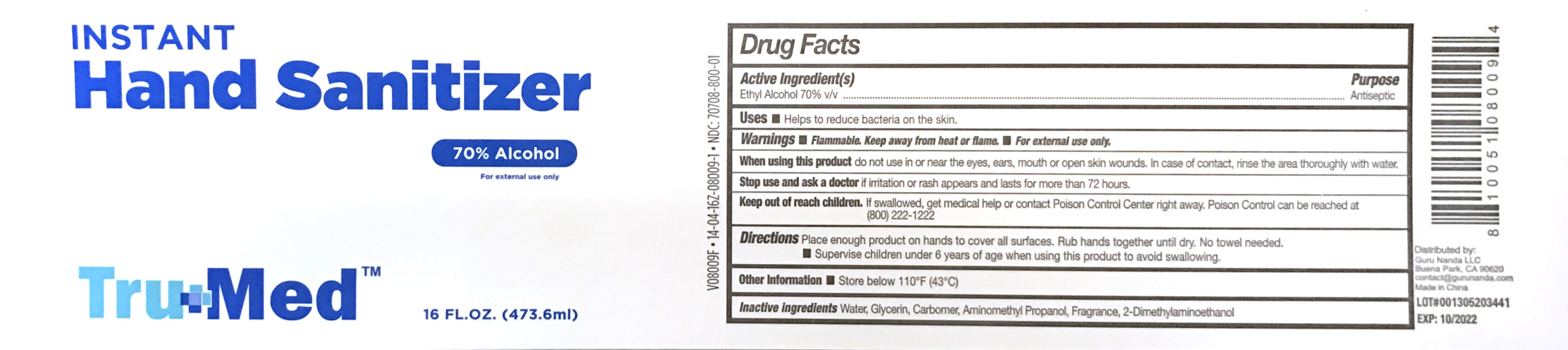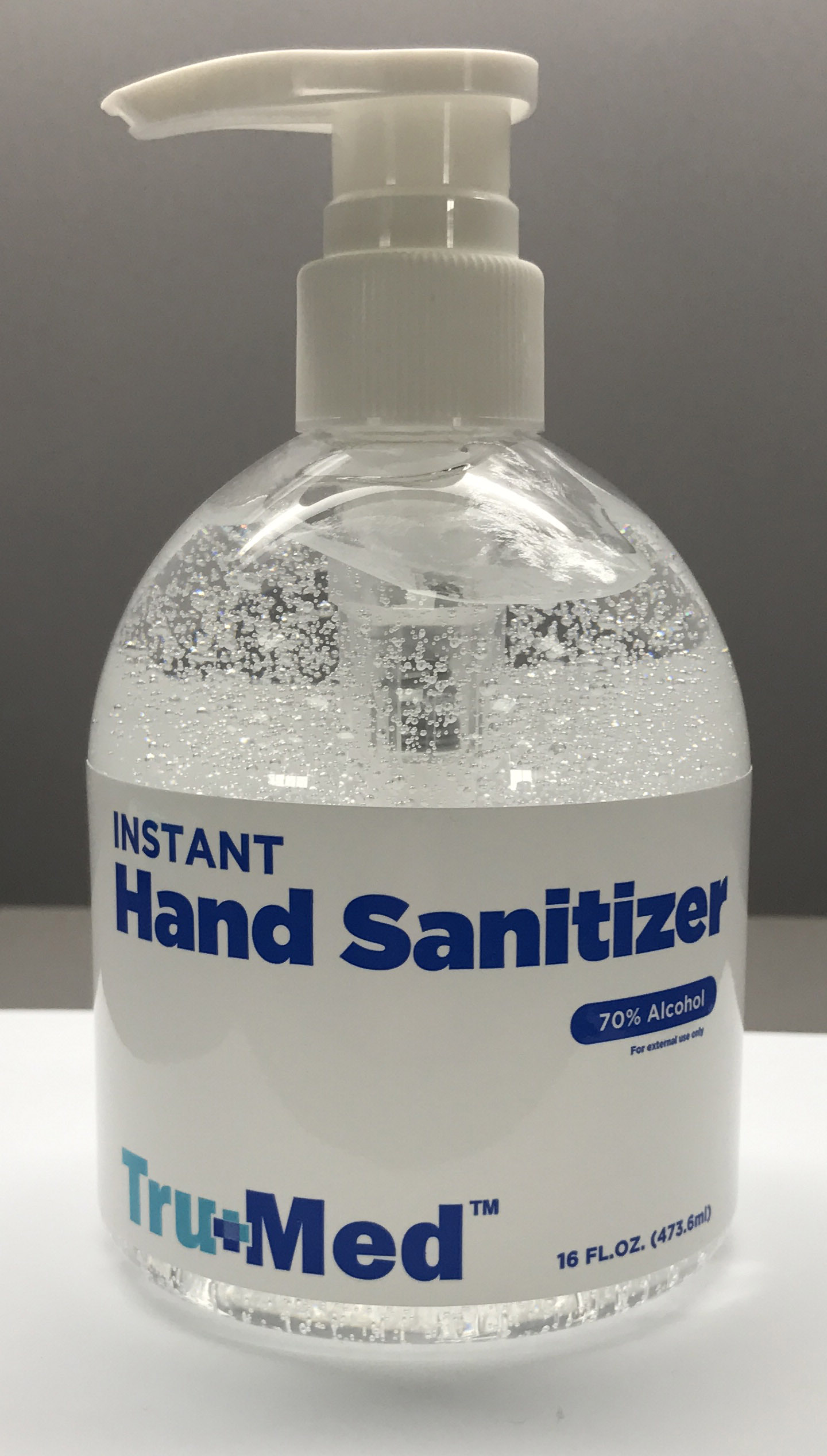 DRUG LABEL: TRUMED Instant Hand Sanitizer
NDC: 70708-800 | Form: GEL
Manufacturer: GURUNANDA LLC
Category: otc | Type: HUMAN OTC DRUG LABEL
Date: 20220831

ACTIVE INGREDIENTS: ALCOHOL 70 mL/473.6 mL
INACTIVE INGREDIENTS: GLYCERIN 1.2 mL/473.6 mL; WATER 28.279 mL/473.6 mL; AMINOMETHYL PROPANEDIOL 0.12 mg/473.6 mL; LAVENDER OIL 0.1 mL/473.6 mL; CARBOMER 940 0.3 mg/473.6 mL; DEANOL 0.001 mL/473.6 mL

TruMed Instant Hand Sanitizer

ACTIVE INGREDIENT

Ethyl Alcohol 70%

PURPOSE

Antiseptic

WARNINGS

FOR EXTERNAL USE ONLY

Flammable. Keep away from heat or flame.

When using this product do not use in or near the eyes,ears, mouth or open skin wounds. In case of contact, rinse the area thoroughly with water.

Stop use and ask a doctor if irritation or rash appears and lasts for more than 72 hours.

Keep out of reach of children. If swallowed, get medical help or contact a Poison Control Center right away. Poison Control can be reached at (800) 222-1222

DOSAGE AND ADMINISTRATION

-Place enough product on hands to cover all surfaces. Rub hands together until dry.

-No towel needed.

-Supervise children under 6 years when using this product to avoid swallowing.

OTHER SAFETY INFORMATION

Store below 110° F (43° C)

INACTIVE INGREDIENT

Water, Glycerin, Carbomer, Aminomethyl Propanol , Fragrance, 2-Dimethylaminoethanol

INDICATIONS AND USAGE

Helps to reduce bacteria on skin